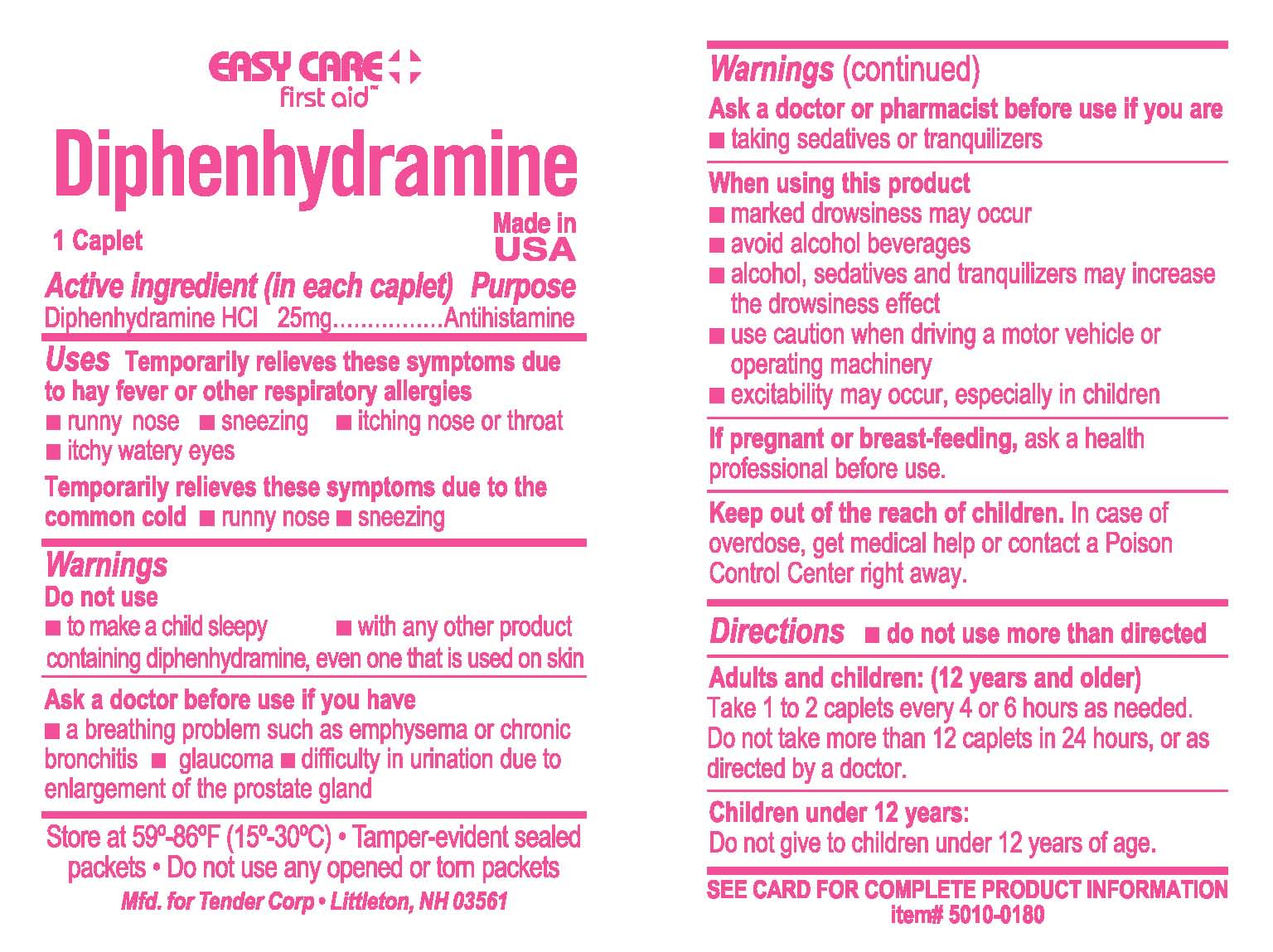 DRUG LABEL: Easy Care First Aid Diphenhydramine
NDC: 44224-0017 | Form: TABLET, FILM COATED
Manufacturer: Tender Corporation
Category: otc | Type: HUMAN OTC DRUG LABEL
Date: 20191003

ACTIVE INGREDIENTS: DIPHENHYDRAMINE HYDROCHLORIDE 25 mg/1 1
INACTIVE INGREDIENTS: CELLULOSE, MICROCRYSTALLINE; CROSCARMELLOSE SODIUM; D&C RED NO. 27; HYPROMELLOSES; LACTOSE; MAGNESIUM STEARATE; POLYETHYLENE GLYCOL, UNSPECIFIED; SILICON DIOXIDE; TITANIUM DIOXIDE

Easy Care First Aid Ibuprofen

Drug Facts

Active ingredient (in each caplet)

Diphenhydramine Hydrochloride 25 mg

Purpose

Antihistamine

Uses

Temporarily relieves these symptoms due to hay fever or other respiratory allergies

- runny nose
- sneezing
- itching nose or throat
- itchy-watery eyes

Temporarily relieves these symptoms due to the common cold

- runny nose
- sneezing

Warnings

Do not use

- to make a child sleepy
- with any other product containing diphenhydramine, even one that is used on skin.

Ask a doctor before use if you have

- a breathing problem such as emphysema or chronic bronchitis
- difficulty in urination due to enlargement of the prostate gland
- glaucoma

Ask a doctor or pharmacist before use if you are

- taking sedatives or tranquilizers

When using this product

- marked drowsiness may occur
- avoid alcohol beverages
- alcohol, sedatives and tranquilizers may increase the drowsiness effect
- use caution when driving a motor vehicle or operating machinery
- excitability may occur, especially in children

If pregnant or breast feeding,

ask a health professional before use.

Keep out of the reach of children.

In case of overdose, contact a physician or poison control center immediately.

Directions

- do not use more than directed

Adults and children: (12 years and older)

Take 1 to 2 caplets every 4 to 6 hours as needed. Do not take more than 12 caplets in 24 hours, or as directed by a doctor.

Children under 12 years:

Do not give to children under 12 years of age.

Other information

- each caplet may contain: calcium 25mg
- protect from light
- use by expiration date on packet
- store at room temperature 59º-86ºF (15º-30ºC
- tamper-evident sealed packets
- do not use any opened or torn packets

Inactive ingredients

carnauba wax*, colloidal silicon dioxide, croscarmellose sodium, D&C red #27, dicalcium phosphate*, hypromellose, lactose*, magnesium stearate, microcrystalline cellulose, polyethylene glycol, polysorbate 80*, titanium dioxide

* may contain

Easy Care First Aid Diphenhydramine

1 Caplet

Made in USA

See card for complete product information